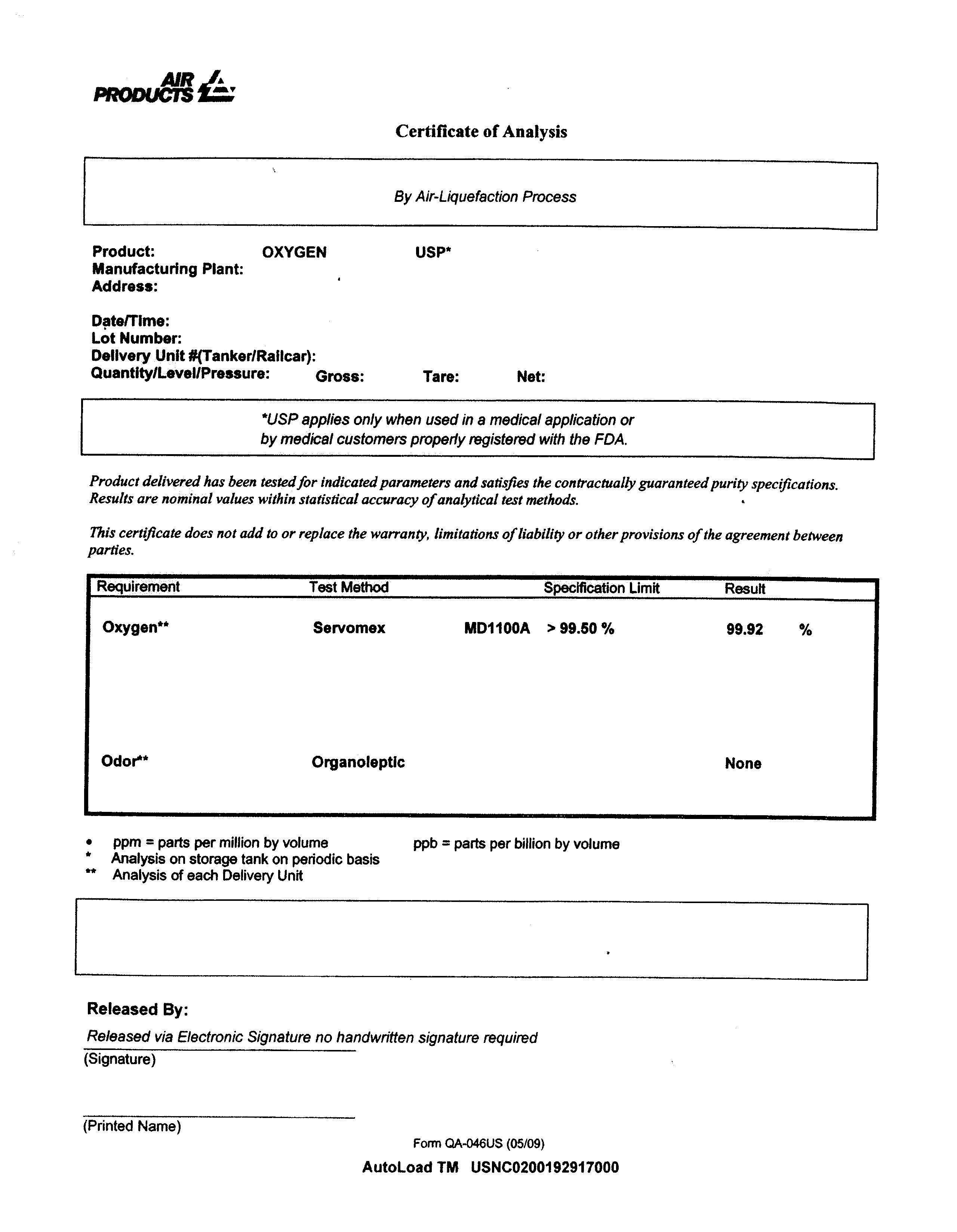 DRUG LABEL: Oxygen
NDC: 10018-8999 | Form: GAS
Manufacturer: Air Products and Chemicals, Inc.
Category: prescription | Type: HUMAN PRESCRIPTION DRUG LABEL
Date: 20160811

ACTIVE INGREDIENTS: Oxygen 990 mL/1 L

PACKAGE LABEL

Oxygen